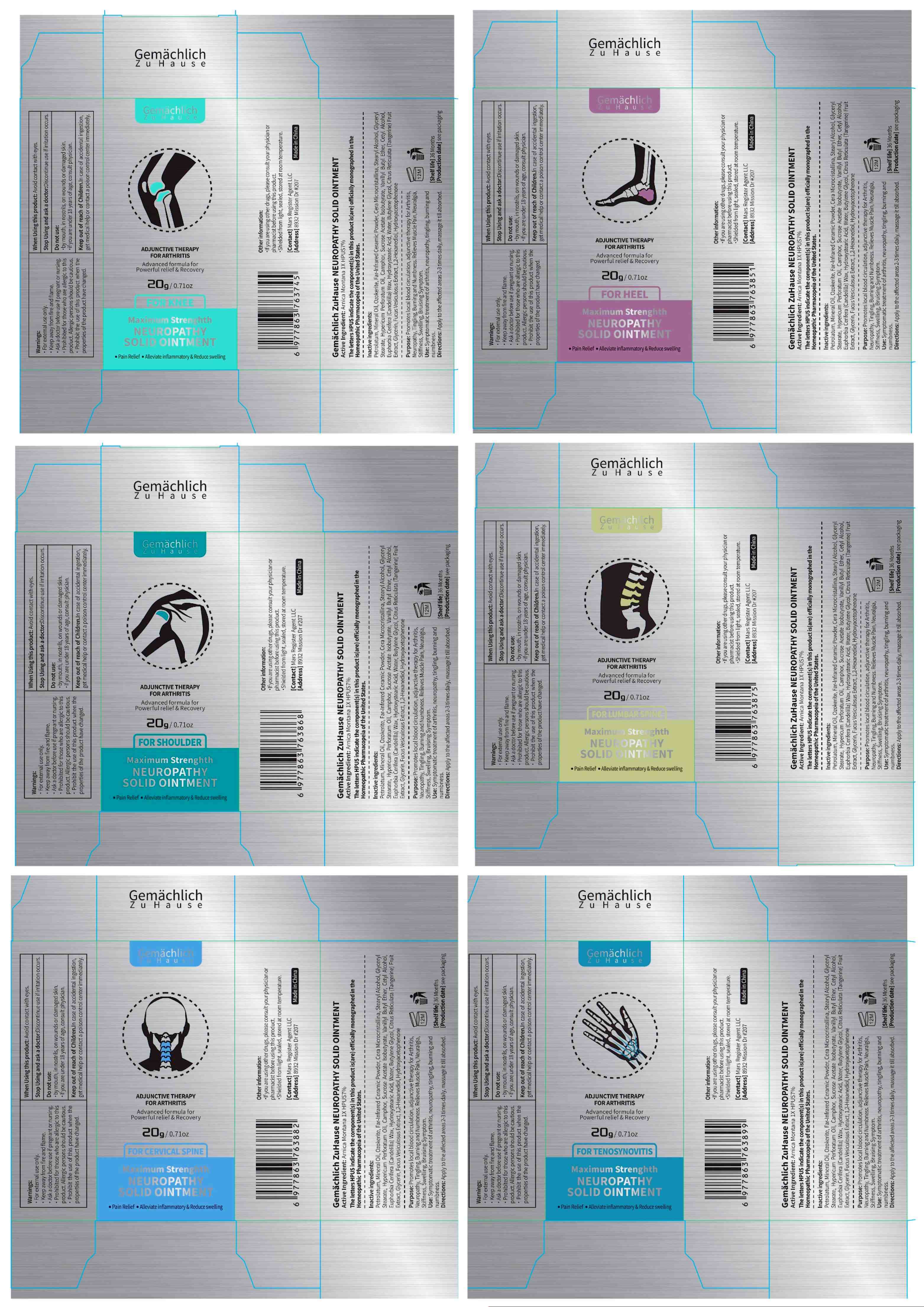 DRUG LABEL: Gemachlich ZuHause NEUROPATHY SOLID Ointment.
NDC: 76986-013 | Form: OINTMENT
Manufacturer: Guangdong Quadrant Ecological Technology Co., Ltd.
Category: otc | Type: HUMAN OTC DRUG LABEL
Date: 20251030

ACTIVE INGREDIENTS: ARNICA MONTANA 7 g/100 g
INACTIVE INGREDIENTS: 12-HYDROXYSTEARIC ACID; WATER; GLYCERYL STEARATE SE; EUPHORBIA CERIFERA (CANDELILLA) WAX; GLYCERIN; FUCUS VESICULOSUS; PETROLATUM; STEARYL ALCOHOL; ETHYLENE DISTEARAMIDE; 1,2-HEXANEDIOL; CITRUS RETICULATA FRUIT OIL; VANILLYL BUTYL ETHER; HYPERICUM PERFORATUM; MINERAL OIL; CERALIFIMOD; CETYL ALCOHOL; HYDROXYACETOPHENONE; SUCROSE ACETATE ISOBUTYRATE; CAMPHOR (SYNTHETIC); BUTYLENE GLYCOL; CERESIN

76986-013

Active Ingredient

ARNICA MONTANA 7%

Purpose

Promotes local blood circulation, adjunctive therapy for Arthritis、Neuropathy,Tingling, Burning and Numbness. Relieves Muscle Pain, Neuralgia, Stiffness,Swelling,Bruising Symptom.

Use

Symptomatic treatment of arthritis,neuropathy,tingling, burning and numbness.

Warnings

· For external use only.
· Keep away from fire and flame.
· Ask a doctor before use if pregnant or nursing.
· Prohibited for those who are allergic to this product. Allergic persons should be cautious.
· Prohibit the use of this product when the properties of the product have changed.

Do not use

·by mouth,in nostrils,on wounds or damaged skin.
·if you are under 18 years of age,consult physician.

When Using

Avoid contact with eyes.

Stop Use

Discontinue use if irritation occurs.

Ask Doctor

Discontinue use if irritation occurs.

Keep Out Of Reach Of Children

In case of accidental ingestion, get medical help or contact a poison control center immediately.

Directions

Apply to the affected areas 2-3 times daily, massage it till absorbed.

Other information

·If you are using other drugs, please consult your physician or pharmacist before using this product.
·Shielded from light, sealed, stored at room temperature.

Inactive ingredients

Petrolatum,Mineral Oil,Ozokerite,Far-Infrared Ceramic Powder,Cera Microcristallina,Stearyl Alcohol,Glyceryl Stearate,Hypericum Perforatum Oil,Camphor,Sucrose Acetate Isobutyrate,Vanillyl Butyl Ether,Cetyl Alcohol,Euphorbia Cerifera (Candelilla) Wax,Hydroxystearic Acid,Water,Butylene Glycol,Citrus Reticulata (Tangerine) Fruit Extract,Glycerin,Fucus Vesiculosus Extract,1,2-Hexanediol,Hydroxyacetophenone